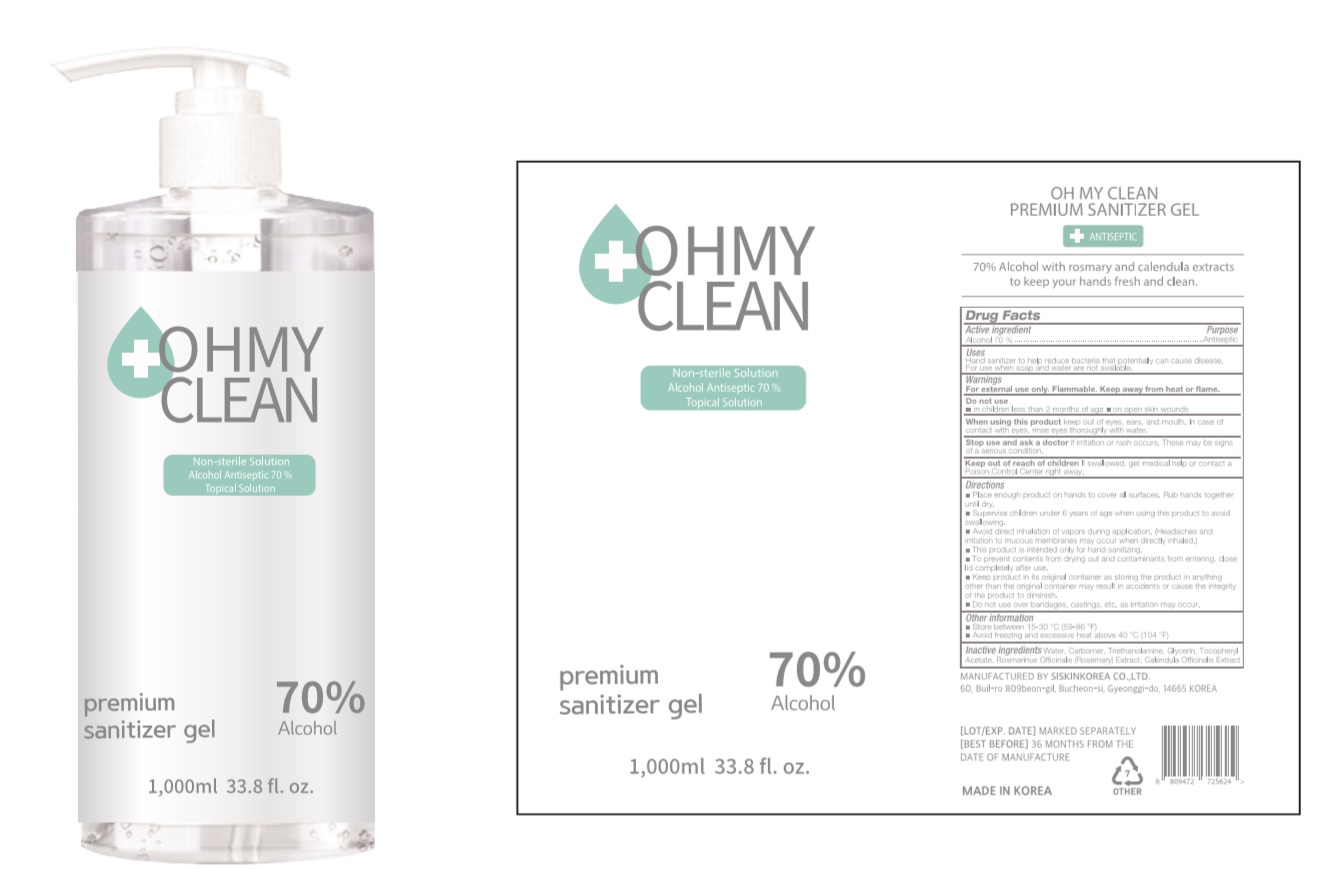 DRUG LABEL: OHMYCLEAN Premium Sanitizer Gel
NDC: 74514-7010 | Form: GEL
Manufacturer: SISKINKOREA CO.,LTD.
Category: otc | Type: HUMAN OTC DRUG LABEL
Date: 20200616

ACTIVE INGREDIENTS: ALCOHOL 700 mL/1000 mL
INACTIVE INGREDIENTS: TROLAMINE; GLYCERIN; .ALPHA.-TOCOPHEROL ACETATE; CALENDULA OFFICINALIS WHOLE; WATER; ROSEMARY; CARBOMER HOMOPOLYMER, UNSPECIFIED TYPE

OHMYCLEAN Premium Sanitizer Gel [74514-7010-1]